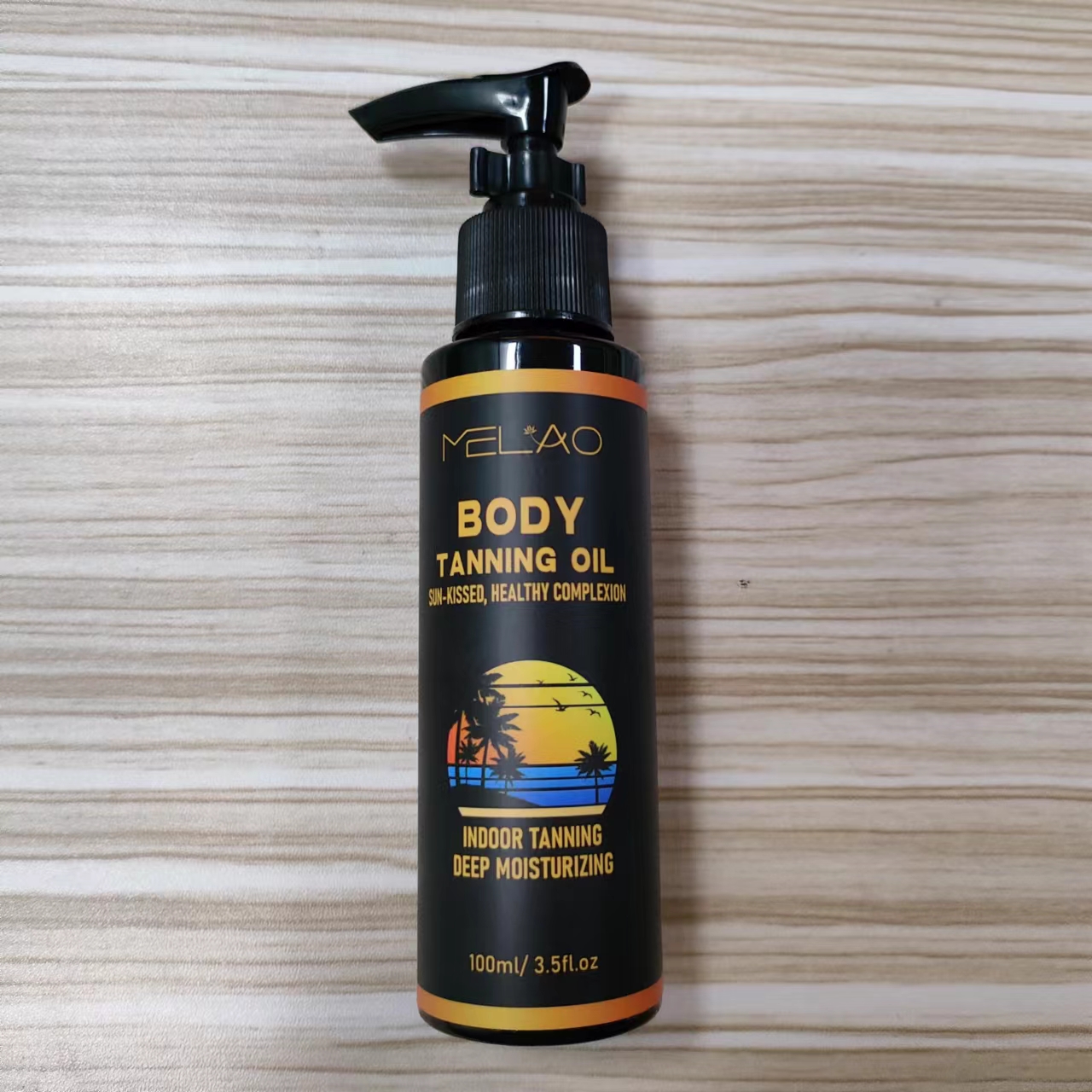 DRUG LABEL: MELAO Body Tanning Oil
NDC: 74458-555 | Form: OIL
Manufacturer: Guangzhou Yilong Cosmetics Co., Ltd
Category: otc | Type: HUMAN OTC DRUG LABEL
Date: 20241028

ACTIVE INGREDIENTS: DIHYDROXYACETONE 10 mg/100 mL
INACTIVE INGREDIENTS: ALOE BARBADENSIS LEAF EXTRACT; HYDROXYACETOPHENONE; PARFUMIDINE; XANTHAN GUM; SODIUM HYALURONATE; STEPHANIA TETRANDRA ROOT; TARAXACUM OFFICINALE LEAF; EDETATE DISODIUM; SAURURUS CHINENSIS FLOWER; HAMAMELIS VIRGINIANA (WITCH HAZEL) LEAF EXTRACT; 1,2-HEXANEDIOL; WATER; PEG-40 HYDROGENATED CASTOR OIL; ERYTHRITOL

MELAO BODY TANNING OIL

ACTIVE INGREDIENT

Dihydroxyacetone

INACTIVE INGREDIENT

Water

Erythritol

Xanthan Gum

Sodium Hyaluronate

Hamamelis Virginiana (Witch Hazel) Extract

Saururus Chinensis Leaf/Root Extract

Aloe Barbadensis Extract

Taraxacum Officinale (Dandelion) Leaf

Extract

Stephania Tetrandra Root Extract

Hydroxyacetophenone

1,2-Hexanediol

Disodium EDTA

PEG-40 Hydrogenated Castor Oil

Parfum

PURPOSE

Body Self-tanning.

INDICATIONS AND USAGE

Apply an appropriate amount evenly on the skin and massage until absorbed.Avoiding sensitive areas.Better results in four hours or more.

WARNINGS

For external use only.

Stop use and ask a doctor if rash occurs.

Do not use on damaged or broken skin.

When using this product keep out of eyes. Rinse with water to remove.

Keep out of reach of children. If swallowed, get medical help or contact a Poison Control Center right away.

DOSAGE AND ADMINISTRATION

Apply an appropriate amount evenly on the skin and massage until absorbed.Avoiding sensitive areas.Better results in four hours or more.